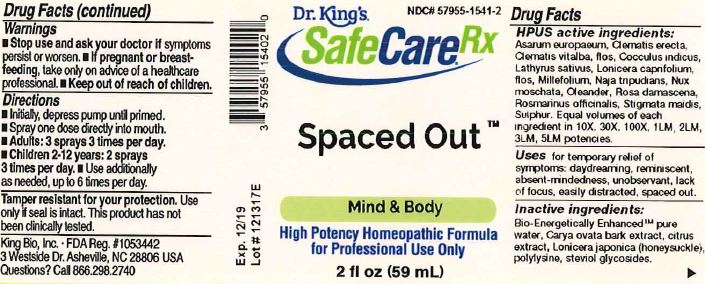 DRUG LABEL: Spaced out
NDC: 57955-1541 | Form: LIQUID
Manufacturer: King Bio Inc.
Category: homeopathic | Type: HUMAN OTC DRUG LABEL
Date: 20180314

ACTIVE INGREDIENTS: ASARUM EUROPAEUM 10 [hp_X]/59 mL; CLEMATIS RECTA FLOWERING TOP 10 [hp_X]/59 mL; CLEMATIS VITALBA FLOWER 10 [hp_X]/59 mL; ANAMIRTA COCCULUS SEED 10 [hp_X]/59 mL; LATHYRUS SATIVAS SEED 10 [hp_X]/59 mL; LONICERA CAPRIFOLIUM FLOWERING TOP 10 [hp_X]/59 mL; ACHILLEA MILLEFOLIUM 10 [hp_X]/59 mL; NAJA NAJA VENOM 10 [hp_X]/59 mL; NUTMEG 10 [hp_X]/59 mL; NERIUM OLEANDER LEAF 10 [hp_X]/59 mL; ROSA DAMASCENA FLOWERING TOP 10 [hp_X]/59 mL; ROSMARINUS OFFICINALIS FLOWERING TOP 10 [hp_X]/59 mL; CORN SILK 10 [hp_X]/59 mL; SULFUR 10 [hp_X]/59 mL
INACTIVE INGREDIENTS: WATER; CARYA OVATA BARK; CITRUS BIOFLAVONOIDS; LONICERA JAPONICA FLOWER; POLYEPSILON-LYSINE (4000 MW); REBAUDIOSIDE A

Spaced Out™

ACTIVE INGREDIENT

Drug Facts__________________________________________________________________________________________________________

HPUS activeingredients: Asarum europaeum, Clematis erecta, Clematis vitalba, flos, Cocculus indicus, Lathyrus sativus, Lonicera caprifolium, flos, Millefolium, Naja tripudians, Nux moschata, Oleander, Rosa damascena, Rosmarinus officinalis, Stigmata maidis, Sulphur. Equal volumes of each ingredient in 10X, 30X, 100X, 1LM, 2LM, 3LM, 5LM potencies.

INDICATIONS AND USAGE

Uses for temporary relief of symptoms: daydreaming, reminiscent, absent-mindedness, unobservant, lack of focus, easily distracted, spaced out.

Inactive Ingredients:

Bio-Energetically Enhanced™ pure water, Carya ovata bark extract, citrus extract, Lonicera japonica (honeysuckle), polylysine, steviol glycosides.

Warnings

- Stop use and ask your doctor if symptoms persist or worsen.
- If pregnant or breast-feeding, take only on advice of a healthcare professional.

- Keep out of reach of children

Directions

- Initially, depress pump until primed.
- Spray one dose directly into mouth.
- Adults: 3 sprays 3 times per day.
- Children 2-12 years: 2 sprays 3 times per day
- Use additionally as needed, up to 6 times per day.

OTHER SAFETY INFORMATION

Tamper resistant for your protection. Use only if safety seal is intact. This product has not been clinically tested.

PURPOSE

Uses for temporary relief of symptoms:

- daydreaming
- reminiscent
- absent-mindedness
- unobservant
- lack of focus
- easily distracted
- spaced out